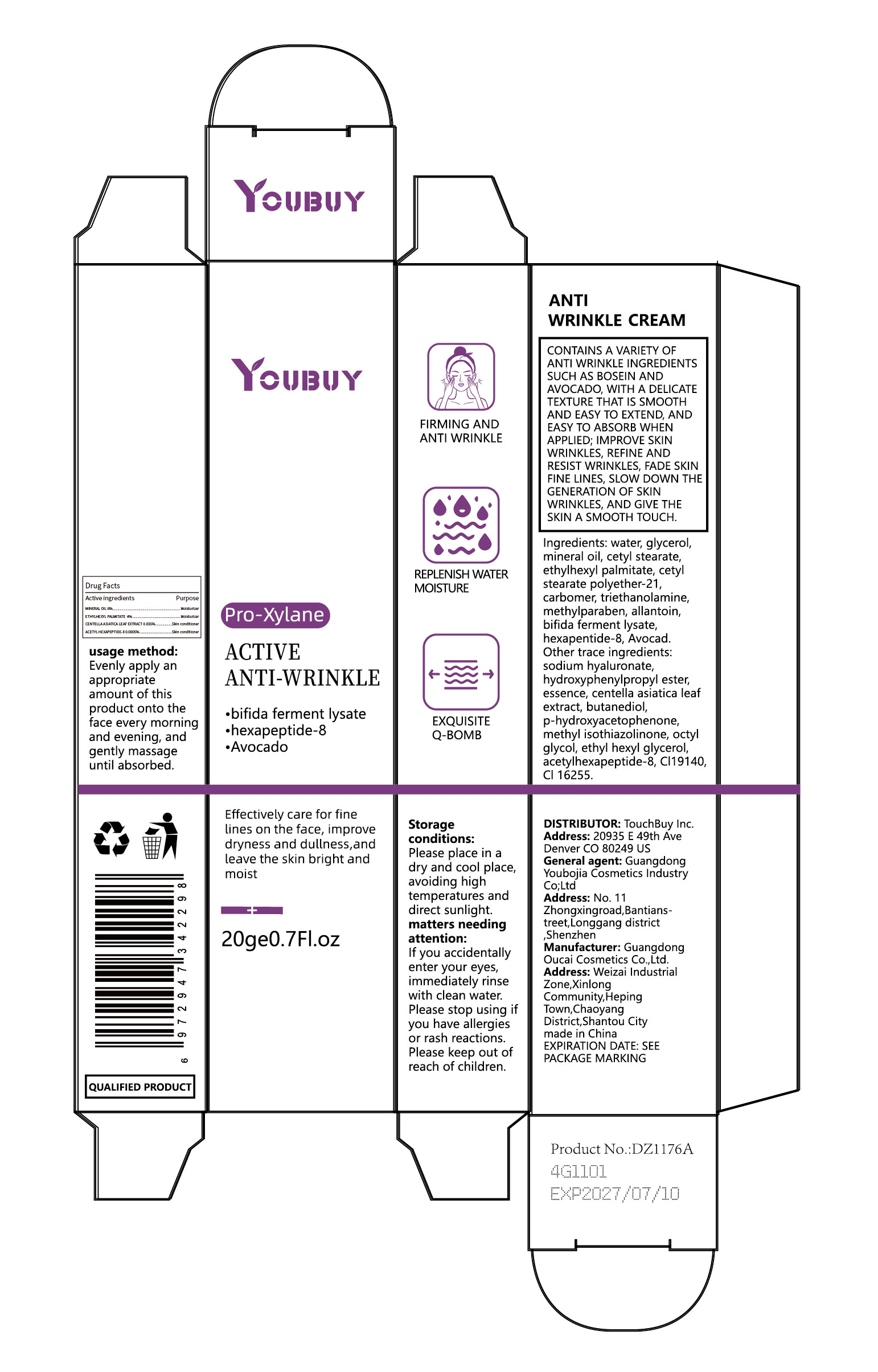 DRUG LABEL: YOUBUY Anti Wrinkle Cream
NDC: 84712-007 | Form: CREAM
Manufacturer: Guangdong Youbaijia Cosmetic Industry Co., Ltd
Category: otc | Type: HUMAN OTC DRUG LABEL
Date: 20240913

ACTIVE INGREDIENTS: MINERAL OIL 1.2 g/20 g; ACETYL HEXAPEPTIDE-8 0.0001 g/20 g; ETHYLHEXYL PALMITATE 0.8 g/20 g; CENTELLA ASIATICA LEAF 0.007 g/20 g
INACTIVE INGREDIENTS: STEARETH-21 0.4 g/20 g

ACTIVE INGREDIENT

MINERAL OIL 6 %
ETHYLHEXYL PALMITATE 4 %
ACETYL HEXAPEPTIDE-8 0.0005%
CENTELLA ASIATICA LEAF EXTRACT 0.035%

DO NOT USE

on damaged or broken skin

Keep away from children. Do not swallow.

PURPOSE

ANTI WRINKLE

QUESTIONS

Contact name: Jessie Peng
Company phone number: +1 818 579 7288
Company e-mail: jessie@registeragentllc.com

STOP USE

Please stop using if you have allergies or rash reactions.

WHEN USING

If you accidentally enter your eyes. immediately rinse with clean water.

INACTIVE INGREDIENT

water
glycerol
cetyl stearate
cetyl stearate polyether-21
carbomer
triethanolamine
methylparaben
allantoin
bifida ferment lysate
Avocad
sodium hyaluronate
hydroxyphenylpropyl ester
essence
p-hydroxyacetophenone
butanediol
methyl isothiazolinone
octyl glycol
ethyl hexy| glycerol
acetylhexapeptide-8
CI19140
Cl 16255

WARNINGS

For external use only.

STORAGE AND HANDLING

Please place in a dry and cool place, avoiding high temperatures and direct sunlight

INDICATIONS AND USAGE

CONTAINS A VARIETY OF ANTI WRINKLE INGREDIENTS SUCH AS BOSEIN AND AVOCADO.WITH A DELICATE TEXTURE THAT IS SMOOTH AND EASY TO EXTEND.AND EASY TO ABSORB WHEN APPLIED: IMPROVE SKIN WRINKLES.REFINE AND RESIST WRINKLES,FADE SION FINE LINES, SLOW DOWN THE GENERATION OF SKIN WRINKLES.AND GIVE THE SKIN A SMOOTH TOUCH.

DOSAGE AND ADMINISTRATION

Evenly apply an appropriate amount of this product onto the face every morning and evening. and gently massage until absorbed.